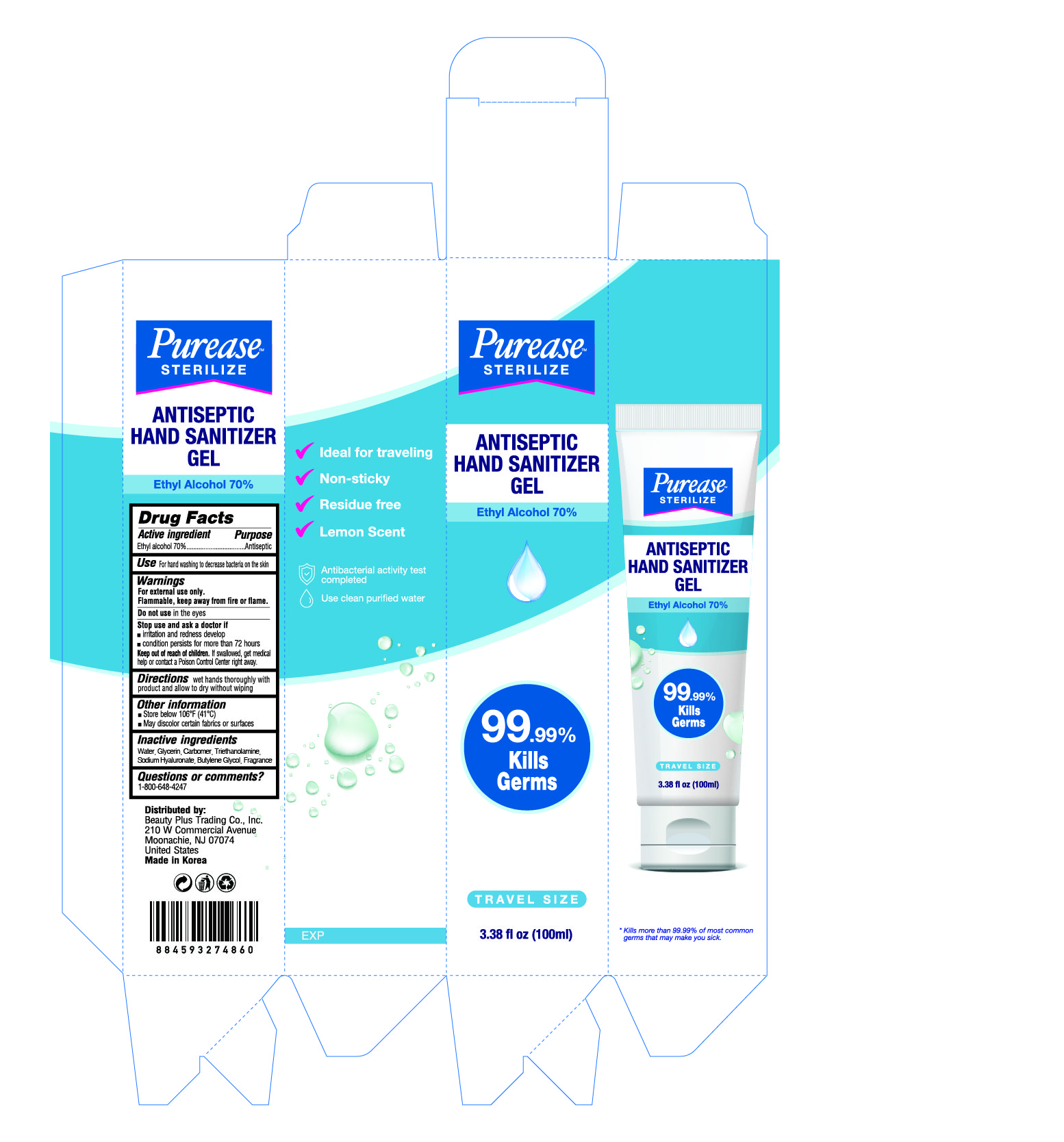 DRUG LABEL: PUREASE ANTISEPTIC HAND SANITIZER Gel
NDC: 74339-1007 | Form: GEL
Manufacturer: PL COSMETIC
Category: otc | Type: HUMAN OTC DRUG LABEL
Date: 20200512

ACTIVE INGREDIENTS: ALCOHOL 70 mL/100 mL
INACTIVE INGREDIENTS: GLYCERIN; CARBOMER HOMOPOLYMER, UNSPECIFIED TYPE; WATER; BUTYLENE GLYCOL; HYALURONATE SODIUM; TROLAMINE

PUREASE ANTISEPTIC HAND SANITIZER Gel 100 ml tube < outerbox: 74339-1007-2